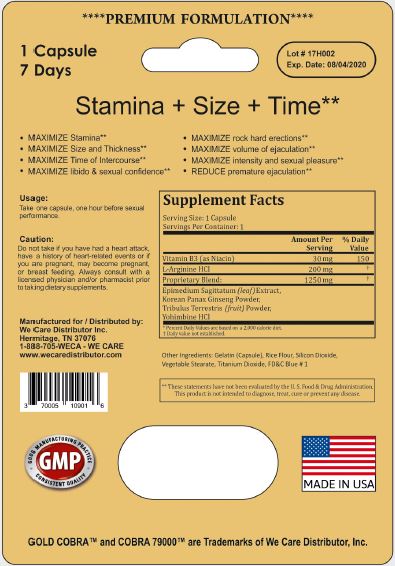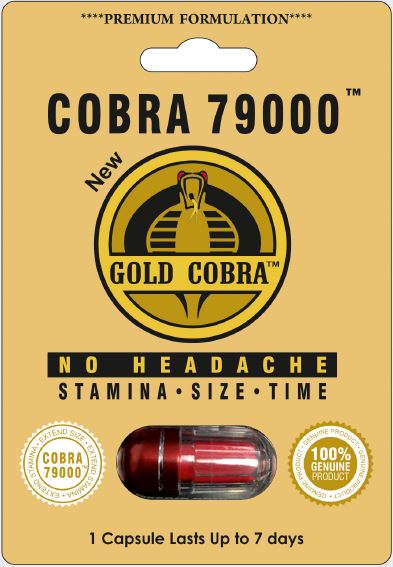 DRUG LABEL: Cobra 79000
NDC: 70005-109 | Form: CAPSULE
Manufacturer: We Care Distributor Inc.
Category: other | Type: DIETARY SUPPLEMENT
Date: 20170925

ACTIVE INGREDIENTS: NIACIN 30 mg/1 1; ARGININE 200 mg/1 1; EPIMEDIUM SAGITTATUM TOP 100 mg/1 1; ASIAN GINSENG 600 mg/1 1; TRIBULUS TERRESTRIS FRUIT 500 mg/1 1; YOHIMBINE HYDROCHLORIDE 50 mg/1 1
INACTIVE INGREDIENTS: GELATIN, UNSPECIFIED; BROWN RICE; SILICON DIOXIDE; GLYCERYL TRISTEARATE; TITANIUM DIOXIDE; FD&C BLUE NO. 1

Cobra 79000 Sexual Enhancer

STATEMENT OF IDENTITY

Men's Sexual Health Supplement

Directions

Take one capsule, one hour before sexual performance.

Warnings

Do not take if you have had a heart attack, have a history of heart-related events or if you are pregnant, may become pregnant, or breast feeding. Avoid this product if you have liver or kidney disease, or high blood pressure. Discontinue use and consult a licensed physician and/or pharmacist if any adverse reactions occur.

Precautions

Always consult with a licensed physician and/or pharmacist prior to taking dietary supplements.

Do not use if either tamper-evident seal is broken or missing.

Keep out of the reach of children.

Store in a cool, dry place.

HEALTH CLAIM

1 Capsule Lasts Up to 7 days

Stamina + Size + Time [These statements have not been evaluated by the Food and Drug Administration. This product is not intended to diagnose, treat, cure, or prevent any disease.]

- MAXIMIZE Stamina
- MAXIMIZE Size and Thickness
- MAXIMIZE Time of Intercorse
- MAXIMIZE libido & sexual confidence
- MAXIMIZE rock hard erections
- MAXIMIZE volume of ejaculation
- MAXIMIZE intensity and sexual pleasure
- REDUCE premature ejaculation

HEALTH CLAIM

Supplement Facts
Serving Size: 1 Capsule
Serving Per Container: 1
 | Amount Per Serving | % Daily Value [Percent Daily Values are based on a 2,000 calories diet.]
Vitamin B3 (as Niacin) | 30 mg | 150
L-Arginine HCl | 200 mg | [Daily value not established.]
Proprietary Blend: | 1250 mg
Epimedium Sagittatum (leaf) Extract,
Korean Panax Ginseng Powder,
Tribulus Terrestris (fruit) Powder,
Yohimbine HCl

Other Ingredients

Gelatin (Capsule), Rice Flour, Silicon Dioxide, Vegetable Stearate, Titanium Dioxide, FD&C Blue # 1

HEALTH CLAIM

Manufactured by:
VitaCare Pharma LLC
South Plainfield, NJ 07080